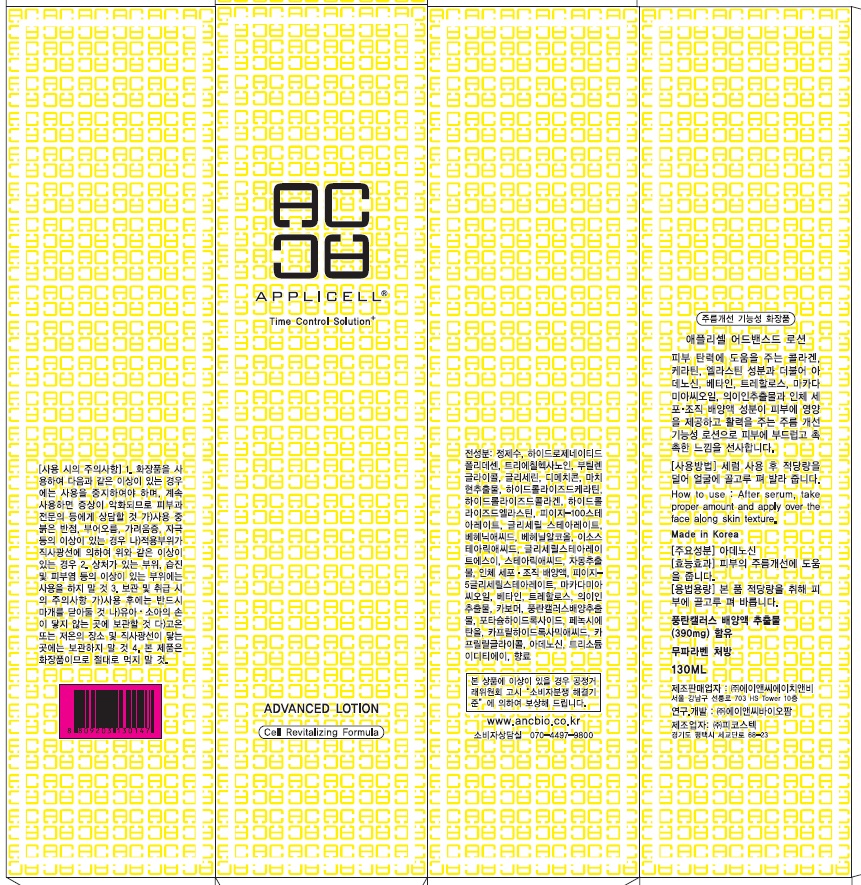 DRUG LABEL: Applicell Advanced
NDC: 71098-010 | Form: LOTION
Manufacturer: Anc HnB Inc.
Category: otc | Type: HUMAN OTC DRUG LABEL
Date: 20161125

ACTIVE INGREDIENTS: Dimethicone 4.55 g/130 mL
INACTIVE INGREDIENTS: Water; Butylene Glycol

ACTIVE INGREDIENT

Active Ingredient: Dimethicone 3.5%

INACTIVE INGREDIENT

Inactive Ingredients: Water, Hydrogenated Polydecene, Triethylhexanoin, Butylene Glycol, Glycerin, Citrus Paradisi (Grapefruit) Fruit Extract, PEG-5 Glyceryl Stearate , PEG-100 Stearate, Glyceryl Stearate, Isostearic Acid, Stearic Acid, Macadamia Ternifolia Seed Oil, Betaine, Trehalose, Glyceryl Stearate SE, Behenic Acid, Behenyl Alcohol, Human fibroblast Conditioned Media, Neofinetia Falcata Callus Culture Extract, Phenoxyethanol, Fragrance, Carbomer, Portulaca Oleracea Extract, Hydrolyzed Keratin, Hydrolyzed Collagen, Hydrolyzed Elastin, Coix Lacryma-Jobi Ma-yuen Seed Extract, Potassium Hydroxide, Trisodium EDTA, Caprylhydroxamic Acid, Caprylyl Glycol

PURPOSE

Purpose: Skin Protectant

WARNINGS

Warnings: For external use only When using this product do not get into eyes, Stop use and ask a doctor if rash occurs Do not use on - deep puncture wounds - animal bites - serious burns Keep out of reach of children

KEEP OUT OF REACH OF CHILDREN

INDICATIONS & USAGE

Indications & usage: APPLICELL Advanced Lotion is available to nourish to the skin and brings a soft, moist feel.

DOSAGE & ADMINISTRATION

How to use: After serum, take proper amount and apply over the face along skin texture.